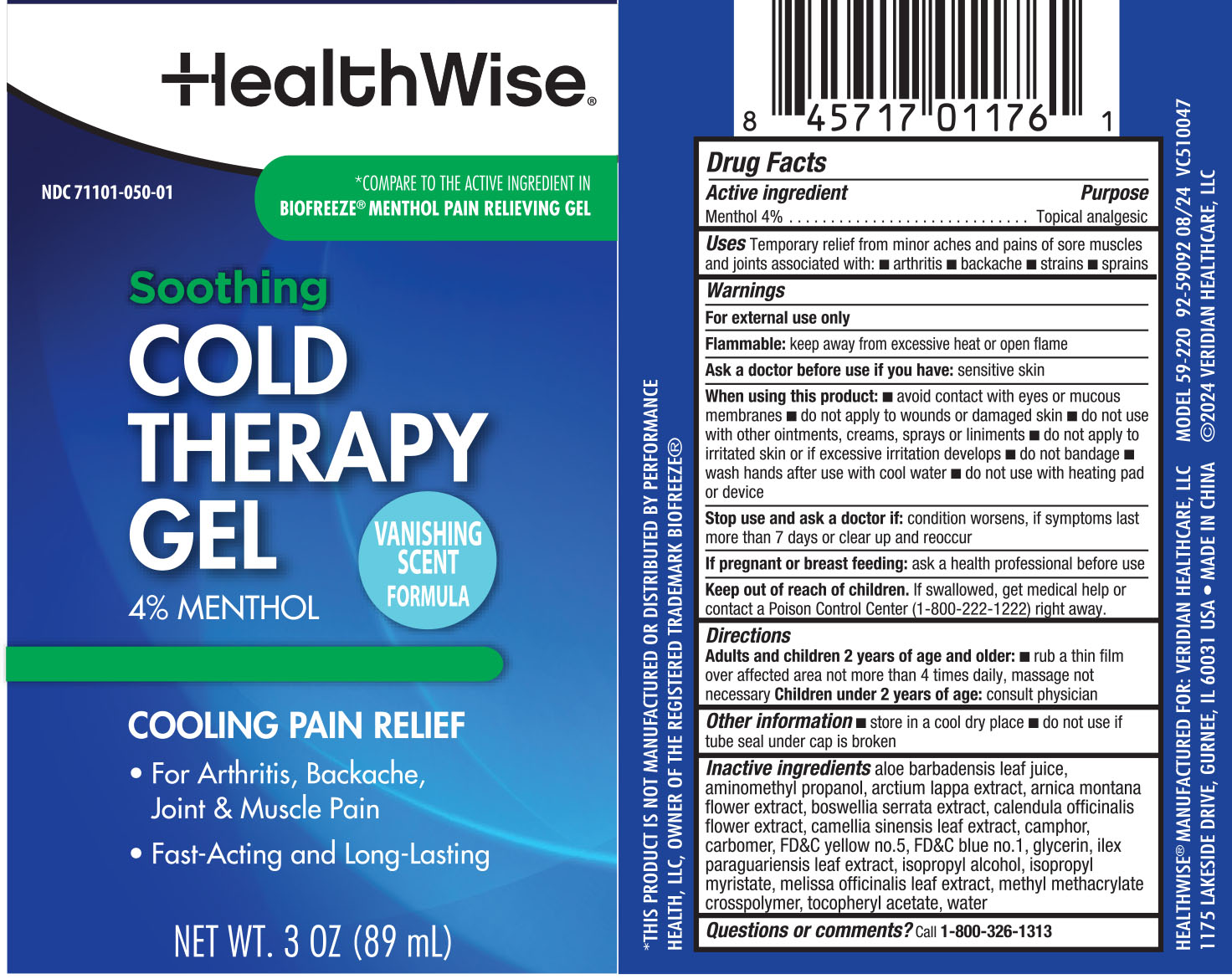 DRUG LABEL: HealthWise Soothing Cold Therapy Gel
NDC: 71101-050 | Form: GEL
Manufacturer: Veridian Healthcare
Category: otc | Type: HUMAN OTC DRUG LABEL
Date: 20240808

ACTIVE INGREDIENTS: MENTHOL 4 g/1 mL
INACTIVE INGREDIENTS: PARAFFIN; CEDAR LEAF OIL; NUTMEG OIL; THYMOL; TURPENTINE OIL; PETROLATUM

HealthWise Soothing Cold Therapy Gel 4% Menthol

Drug Facts

Active ingredients

Menthol 4%

Purpose

Topical analgesic

Uses

Uses Temporary relief from minor aches and pains of sore muscles and joints associated with:

■arthritis ■backache ■strains■sprains

Warnings

For external use only

Flammable: keep away from excessive heat or open flame

Ask a doctor before use if you have

- sensitive skin

When using this product, do not

When using this product:

■ avoid contact with eyes or mucous membranes

■ do not apply to wounds or damaged skin

■ do not use with other ointments, creams, sprays
or liniments

■do not apply to irritated skin or if excessive irritation develops

■do not bandage

■ wash hands after use with cool water

■do not use with a heating pad or device

Stop use and ask a doctor if: the condition worsens, if the symptoms last more than 7 days or clear up and reoccur

PREGNANCY OR BREAST FEEDING

If pregnant or breast-feeding, ask a health professional before use.

Keep out of reach of children. In case of accidental ingestion, get medical help or contact a Poison Control Center (800-222-1222) right away.

Directions

Adults and children 2 years of age and older:■rub a thin film over affected area not more than 4 times daily, massage not necessary Children under 2 years of age: consult physician

Other information

- store in a cool dry place
- do not use if tube seal under cap is broken

Inactive ingredients

Inactive ingredients aloe barbadensis leaf juice, aminomethyl propanol,arctium lappa extract, arnica montana flower extract, Boswellia serrata extract, calendula officinalis flower extract, camellia sinensis leaf extract, camphor, carbomer, FD&Cyellow
no.5, FD&C blue no.1, glycerin, ilex paraguariensis leaf extract, isopropyl alcohol,isopropyl myristate, melissa officinalis leaf extract, methyl methacrylate crosspolymer, tocopheryl acetate, water